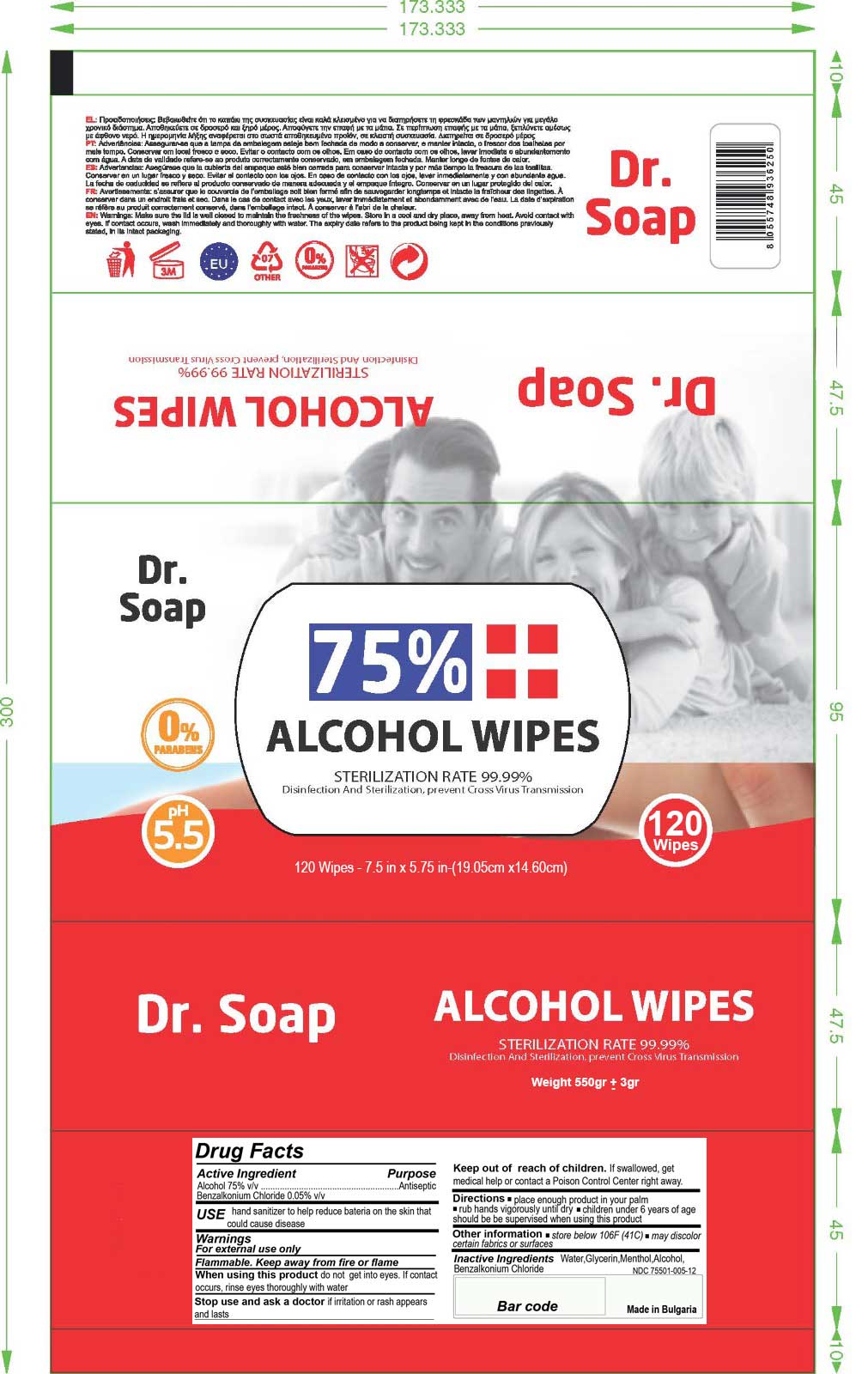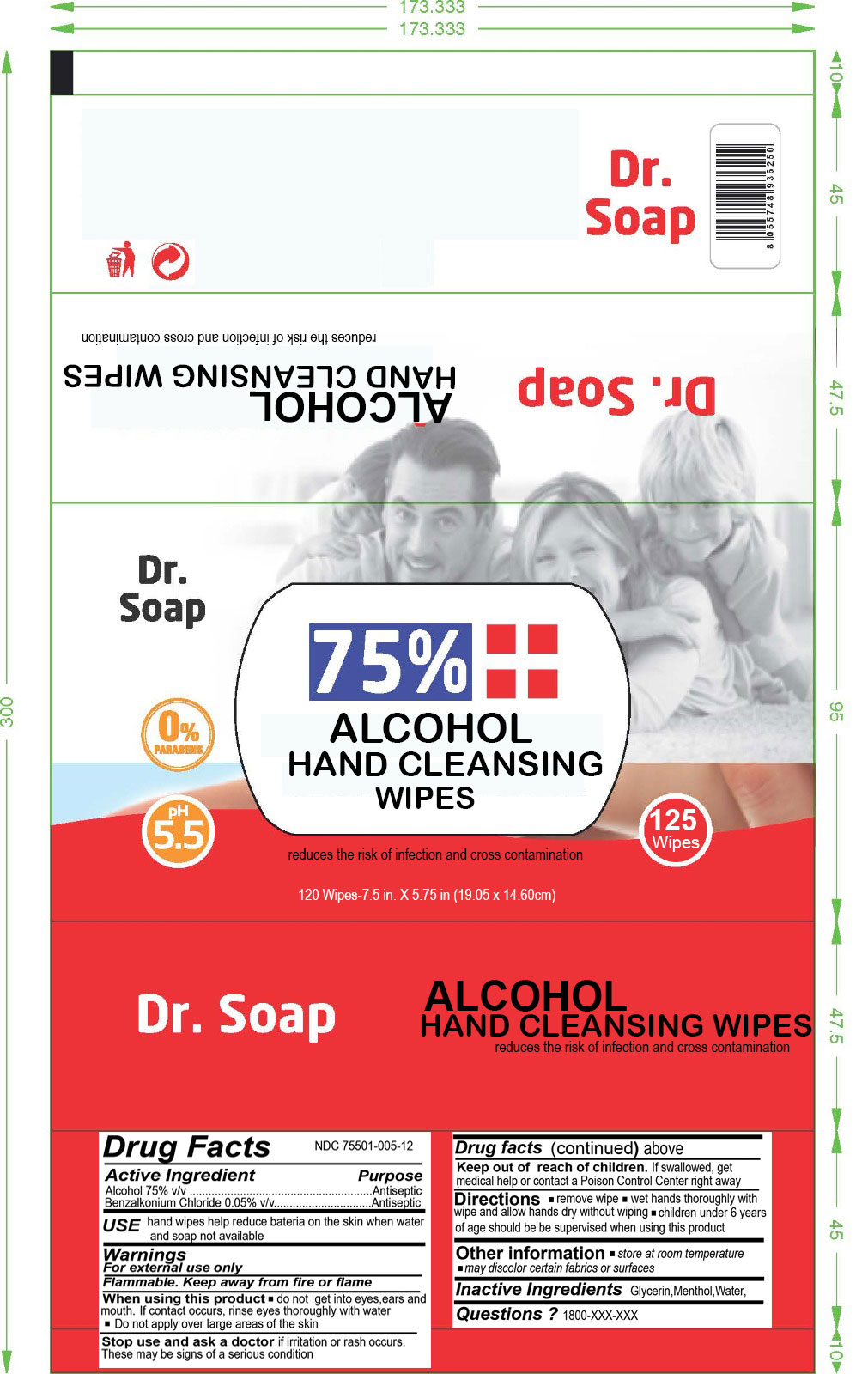 DRUG LABEL: Alcohol Hand Wipe
NDC: 75501-005 | Form: CLOTH
Manufacturer: Eclectic Trade
Category: otc | Type: HUMAN OTC DRUG LABEL
Date: 20200604

ACTIVE INGREDIENTS: BENZALKONIUM CHLORIDE 0.05 g/100 g; ALCOHOL 75 g/100 g
INACTIVE INGREDIENTS: GLYCERIN 0.3 g/100 g; MENTHOL 0.2 g/100 g; WATER 24.45 g/100 g

The alcohol hand cleansing wipe is manufactured using only the following United States Pharmacopoeia (USP) grade ingredients in the preparation of the product

1. Alcohol (ethanol) (USP or Food Chemical Codex (FCC) grade) (75%, volume/volume (v/v))
2. Benzalkonium chloride(0.05% volume/volume (v/v))
3. Water
4. Menthol
5. Glycerin

The firm does not add other active or inactive ingredients. Different or additional ingredients may impact the quality and potency of the product.

Active Ingredient(s)

Alcohol 75% v/v. , Benzalkonium Chloride (0.05% v/v) Purpose: Antiseptic

Purpose

Alcohol Hand Wipe

Use

Alchohol Hand Wipe to help reduce bacteria on the skin when soap and water are not available.

Warnings

For external use only. Flammable. Keep away from heat or flame

Do not use

- in children less than 2 months of age
- on open skin wounds

- When using this product keep out of eyes, ears, and mouth. In case of contact with eyes, rinse eyes thoroughly with water.
- Stop use and ask a doctor if irritation or rash occurs. These may be signs of a serious condition.
- Keep out of reach of children. If swallowed, get medical help or contact a Poison Control Center right away.
- Do not apply large areas of skin

Stop use and ask a doctor if irritation or rash occurs. These may be signs of a serious condition.

Keep out of reach of children. If swallowed, get medical help or contact a Poison Control Center right away.

Directions

- Remove wipe
- Wet hands thoroughly with wipe and allow hands dry without wiping.
- Supervise children under 6 years of age when using this product to avoid swallowing.

RECENT MAJOR CHANGES

- Remove wipe
- Wet hands thoroughly with wipe and allow hands dry without wiping.
- Supervise children under 6 years of age when using this product to avoid swallowing.

Other information

- Store at room temprature
- May discolor certian fabrics or surfaces

Inactive ingredients

Water,Menthol,Glycerin

Package Label - Principal Display Panel

550gr NDC: 75501-005-12